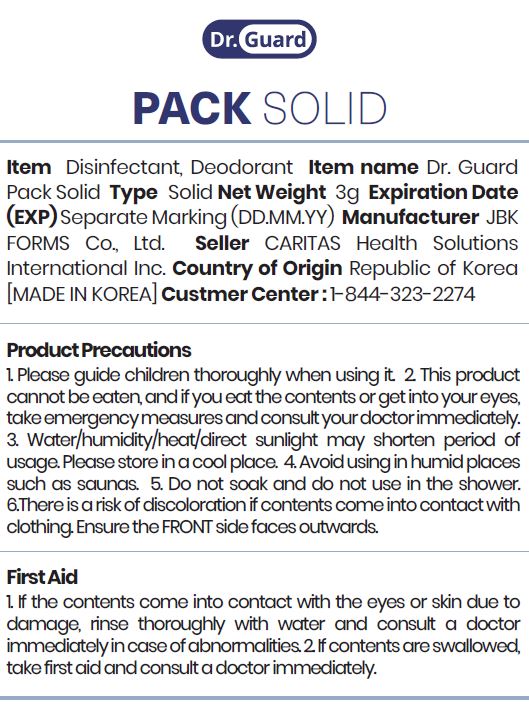 DRUG LABEL: Dr. Guard Pack Solid
NDC: 82358-0005 | Form: POWDER
Manufacturer: JBK FORMS Co Ltd
Category: otc | Type: HUMAN OTC DRUG LABEL
Date: 20211107

ACTIVE INGREDIENTS: SODIUM CHLORITE 10 g/100 g
INACTIVE INGREDIENTS: CITRIC ACID MONOHYDRATE

Drug Facts

ACTIVE INGREDIENT

sodium chlorite

INACTIVE INGREDIENT

citric acid, water

PURPOSE

Disinfectant · Deodorizer

KEEP OUT OF REACH OF THE CHILDREN

INDICATIONS AND USAGE

How to Use (How to Activate)
- The stick contains a main liquid solution and an ampoule inside that includes active
ingredients in powder form.
Bend the middle part of the stick to break the ampoule.
Once the ampoule inside the stick cracks, sufficiently shake the stick to mix the powder
with the solution well.
As it turns yellow, the stick is activated and the pure chlorine dioxide is released through
the surface of the stick.
After 3~4 weeks of usage, the stick will turn transparent which indicates that it is no
longer effective. Please dispose the used stick into a general trash bag.

WARNINGS

■ For external use only.

■ Do not use in eyes.

■ lf swallowed, get medical help promptly.

■ Stop use, ask doctor lf irritation occurs.

■ Keep out of reach of children.

DOSAGE AND ADMINISTRATION

for external use only